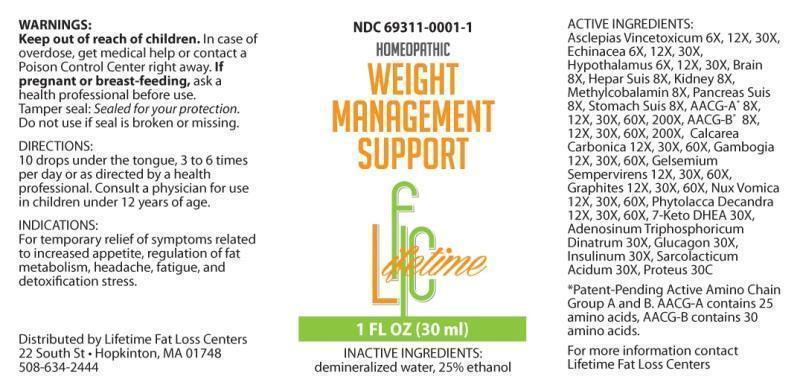 DRUG LABEL: WEIGHT MANAGEMENT SUPPORT
NDC: 69311-0001 | Form: LIQUID
Manufacturer: Lifetime Fat Loss Centers
Category: homeopathic | Type: HUMAN OTC DRUG LABEL
Date: 20150217

ACTIVE INGREDIENTS: CYNANCHUM VINCETOXICUM ROOT 6 [hp_X]/1 mL; ECHINACEA ANGUSTIFOLIA 6 [hp_X]/1 mL; SUS SCROFA HYPOTHALAMUS 6 [hp_X]/1 mL; PORK BRAIN 8 [hp_X]/1 mL; PORK LIVER 8 [hp_X]/1 mL; PORK KIDNEY 8 [hp_X]/1 mL; METHYLCOBALAMIN 8 [hp_X]/1 mL; SUS SCROFA PANCREAS 8 [hp_X]/1 mL; SUS SCROFA STOMACH 8 [hp_X]/1 mL; APC-356433 8 [hp_X]/1 mL; APC-356434 8 [hp_X]/1 mL; OYSTER SHELL CALCIUM CARBONATE, CRUDE 12 [hp_X]/1 mL; GAMBOGE 12 [hp_X]/1 mL; GELSEMIUM SEMPERVIRENS ROOT 12 [hp_X]/1 mL; GRAPHITE 12 [hp_X]/1 mL; STRYCHNOS NUX-VOMICA SEED 12 [hp_X]/1 mL; PHYTOLACCA AMERICANA ROOT 12 [hp_X]/1 mL; 7-KETO-DEHYDROEPIANDROSTERONE 30 [hp_X]/1 mL; ADENOSINE TRIPHOSPHATE DISODIUM 30 [hp_X]/1 mL; GLUCAGON 30 [hp_X]/1 mL; INSULIN PORK 30 [hp_X]/1 mL; LACTIC ACID, L- 30 [hp_X]/1 mL; PROTEUS VULGARIS 30 [hp_C]/1 mL
INACTIVE INGREDIENTS: WATER; ALCOHOL

DRUG FACTS:

ACTIVE INGREDIENTS:

ASCLEPIAS VINCETOXICUM 6X, 12X, 30X, ECHINACEA (ANGUSTIFOLIA) 6X, 12X, 30X, HYPOTHALAMUS (SUIS) 6X, 12X, 30X, BRAIN (SUIS) 8X, HEPAR SUIS 8X, KIDNEY (SUIS) 8X, METHYLCOBALAMIN 8X, PANCREAS SUIS 8X, STOMACH (SUIS) 8X, AACG-A* 8X, 12X, 30X, 60X, 200X, AACG-B* 8X, 12X, 30X, 60X, 200X, CALCAREA CARBONICA 12X, 30X, 60X, GAMBOGIA 12X, 30X, 60X, GELSEMIUM SEMPERVIRENS 12X, 30X, 60X, GRAPHITES 12X, 30X, 60X, NUX VOMICA 12X, 30X, 60X, PHYTOLACCA DECANDRA 12X, 30X, 60X, 7-KETO DHEA (DEHYDROEPIANDROSTERONE) 30X, ADENOSINUM TRIPHOSPHORICUM DINATRUM 30X, GLUCAGON 30X, INSULINUM 30X, SARCOLACTICUM ACIDUM 30X, PROTEUS (VULGARIS) 30C

INDICATIONS:

For temporary relief of symptoms related to increased appetite, regulation of fat, metabolism, headache, fatigue, and detoxification stress.

WARNINGS:

Keep out of reach of children. In case of overdose, get medical help or contact a Poison Control Center right away.

If pregnant or breast-feeding, ask a health professional before use.

Tamper seal: Sealed for your protection.

Do not use if seal is broken or missing.

Keep out of reach of children. In case of overdose, get medical help or contact a Poison Control Center right away.

DIRECTIONS:

10 drops under the tongue, 3 to 6 times per day or as directed by a health professional. Consult a physician for use in children under 12 years of age.

INDICATIONS:

For temporary relief of symptoms related to increased appetite, regulation of fat, metabolism, headache, fatigue, and detoxification stress.

INACTIVE INGREDIENTS:

demineralized water, 25% ethanol

QUESTIONS:

Distributed by Lifetime Fat Loss Centers

22 South St • Hopkinton, MA 01748

508-634-2444

*Patent Pending Active Amino Acid Chain Group A & B

AACG-A contains 25 amino acids

AACG-B contains 30 amino acids

For more information contact Lifetime Fat Loss Centers

PACKAGE LABEL DISPLAY:

NDC 69311-0001-1

HOMEOPATHIC

WEIGHT

MANAGEMENT

SUPPORT

1 FL OZ (30 ml)